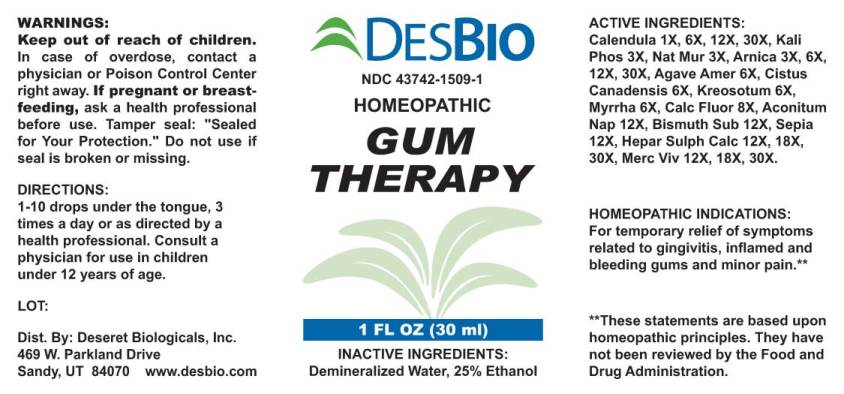 DRUG LABEL: Gum Therapy
NDC: 43742-1509 | Form: LIQUID
Manufacturer: Deseret Biologicals
Category: homeopathic | Type: HUMAN OTC DRUG LABEL
Date: 20230719

ACTIVE INGREDIENTS: CALENDULA OFFICINALIS FLOWERING TOP 1 [hp_X]/1 mL; DIBASIC POTASSIUM PHOSPHATE 3 [hp_X]/1 mL; SODIUM CHLORIDE 3 [hp_X]/1 mL; ARNICA MONTANA 6 [hp_X]/1 mL; AGAVE AMERICANA LEAF 6 [hp_X]/1 mL; HELIANTHEMUM CANADENSE 6 [hp_X]/1 mL; WOOD CREOSOTE 6 [hp_X]/1 mL; MYRRH 8 [hp_X]/1 mL; CALCIUM FLUORIDE 12 [hp_X]/1 mL; ACONITUM NAPELLUS 12 [hp_X]/1 mL; BISMUTH SUBNITRATE 12 [hp_X]/1 mL; SEPIA OFFICINALIS JUICE 12 [hp_X]/1 mL; CALCIUM SULFIDE 12 [hp_X]/1 mL; MERCURY 12 [hp_X]/1 mL
INACTIVE INGREDIENTS: WATER; ALCOHOL

Drug Facts:

ACTIVE INGREDIENTS:

Calendula Officinalis 1X, 6X, 12X, 30X, Kali Phosphoricum 3X, Natrum Muriaticum 3X, Arnica Montana 3X, 6X, 12X, 30X, Agave Americana 6X, Cistus Canadensis 6X, Kreosotum 6X, Myrrha 6X, Calcarea Fluorica 8X, Aconitum Napellus 12X, Bismuthum Subnitricum 12X, Sepia 12X, Hepar Sulphuris Calcareum 12X, 18X, 30X, Mercurius Vivus 12X, 18X, 30X.

HOMEOPATHIC INDICATIONS:

For temporary relief of symptoms related to gingivitis, inflamed and bleeding gums and minor pain.**

**These statements are based upon traditional homeopathic principles. They have not been reviewed by the Food and Drug Administration.

WARNINGS:

Keep out of reach of children. In case of overdose, Contact physician or Poison Control Center right away.

If pregnant or breast-feeding, seek advice of a health professional before use.

Tamper seal: "Sealed for Your Protection." Do not use if seal is broken or missing.

Keep out of reach of children. In case of overdose, contact physician or Poison Control Center right away.

DIRECTIONS:

1-10 drops under the tongue, 3 times a day or as directed by a health professional. Consult a physician for use in children under 12 years of age.

HOMEOPATHIC INDICATIONS:

For temporary relief of symptoms related to gingivitis, inflamed and bleeding gums and minor pain.**

**These statements are based upon traditional homeopathic principles. They have not been reviewed by the Food and Drug Administration.

INACTIVE INGREDIENTS:

Demineralized Water, 25% Ethanol.

QUESTIONS:

Dist. By: Deseret Biologicals, Inc.

469 W. Parkland Drive

Sandy, UT 84070 www.desbio.com

PACKAGE LABEL DISPLAY:

DESBIO
NDC 43742-1509-1
HOMEOPATHIC
GUM
THERAPY
1 FL OZ (30 ml)